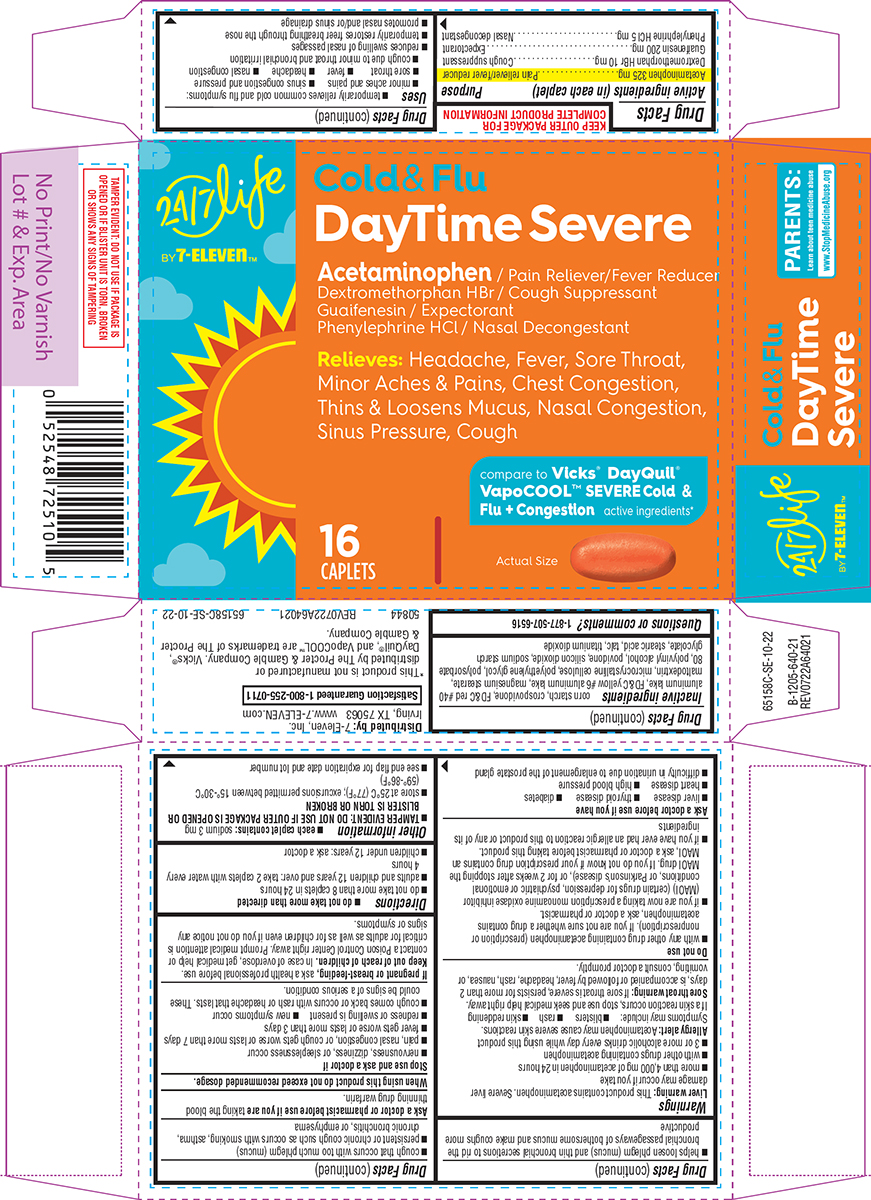 DRUG LABEL: Cold and Flu
NDC: 50844-640 | Form: TABLET, FILM COATED
Manufacturer: L.N.K. International, Inc.
Category: otc | Type: HUMAN OTC DRUG LABEL
Date: 20260127

ACTIVE INGREDIENTS: ACETAMINOPHEN 325 mg/1 1; DEXTROMETHORPHAN HYDROBROMIDE 10 mg/1 1; GUAIFENESIN 200 mg/1 1; PHENYLEPHRINE HYDROCHLORIDE 5 mg/1 1
INACTIVE INGREDIENTS: STARCH, CORN; CROSPOVIDONE, UNSPECIFIED; FD&C RED NO. 40 ALUMINUM LAKE; FD&C YELLOW NO. 6 ALUMINUM LAKE; MAGNESIUM STEARATE; MALTODEXTRIN; MICROCRYSTALLINE CELLULOSE; POLYETHYLENE GLYCOL, UNSPECIFIED; POLYSORBATE 80; POLYVINYL ALCOHOL, UNSPECIFIED; POVIDONE, UNSPECIFIED; SILICON DIOXIDE; SODIUM STARCH GLYCOLATE TYPE A POTATO; STEARIC ACID; TALC; TITANIUM DIOXIDE

Convenience Valet 44-640

Active ingredients (in each caplet)

Acetaminophen 325 mg
Dextromethorphan HBr 10 mg
Guaifenesin 200 mg
Phenylephrine HCl 5 mg

Purpose

Pain reliever/fever reducer
Cough suppressant
Expectorant
Nasal decongestant

Uses

- temporarily relieves common cold and flu symptoms:
  - minor aches and pains
  - sinus congestion and pressure
  - sore throat
  - fever
  - headache
  - nasal congestion
  - cough due to minor throat and bronchial irritation
- reduces swelling of nasal passages
- temporarily restores freer breathing through the nose
- promotes nasal and/or sinus drainage
- helps loosen phlegm (mucus) and thin bronchial secretions to rid the bronchial passageways of bothersome mucus and make coughs more productive

Warnings

Liver warning: This product contains acetaminophen. Severe liver damage may occur if you take

- more than 4,000 mg of acetaminophen in 24 hours
- with other drugs containing acetaminophen
- 3 or more alcoholic drinks every day while using this product

Allergy alert: Acetaminophen may cause severe skin reactions. Symptoms may include:

- blisters
- rash
- skin reddening

If a skin reaction occurs, stop use and seek medical help right away.

Sore throat warning: If sore throat is severe, persists for more than 2 days, is accompanied or followed by fever, headache, rash, nausea, or vomiting, consult a doctor promptly.

Do not use

- with any other drug containing acetaminophen (prescription or nonprescription). If you are not sure whether a drug contains acetaminophen, ask a doctor or pharmacist.
- if you are now taking a prescription monoamine oxidase inhibitor (MAOI) (certain drugs for depression, psychiatric or emotional conditions, or Parkinson’s disease), or for 2 weeks after stopping the MAOI drug. If you do not know if your prescription drug contains an MAOI, ask a doctor or pharmacist before taking this product.
- if you have ever had an allergic reaction to this product or any of its ingredients

Ask a doctor before use if you have

- liver disease
- thyroid disease
- diabetes
- heart disease
- high blood pressure
- difficulty in urination due to enlargement of the prostate gland
- cough that occurs with too much phlegm (mucus)
- persistent or chronic cough such as occurs with smoking, asthma, chronic bronchitis, or emphysema

Ask a doctor or pharmacist before use if you are

taking the blood thinning drug warfarin.

When using this product

do not exceed recommended dosage.

Stop use and ask a doctor if

- nervousness, dizziness, or sleeplessness occur
- pain, nasal congestion, or cough gets worse or lasts more than 7 days
- fever gets worse or lasts more than 3 days
- redness or swelling is present
- new symptoms occur
- cough comes back or occurs with rash or headache that lasts. These could be signs of a serious condition.

If pregnant or breast-feeding,

ask a health professional before use.

Keep out of reach of children.

In case of overdose, get medical help or contact a Poison Control Center right away. Prompt medical attention is critical for adults as well as for children even if you do not notice any signs or symptoms.

Directions

- do not take more than directed
- do not take more than 8 caplets in 24 hours
- adults and children 12 years and over: take 2 caplets with water every 4 hours
- children under 12 years: ask a doctor

Other information

- each caplet contains: sodium 3 mg
- TAMPER EVIDENT: DO NOT USE IF OUTER PACKAGE IS OPENED OR BLISTER IS TORN OR BROKEN
- store at 25°C (77°F); excursions permitted between 15°-30°C (59°-86°F)
- see end flap for expiration date and lot number

Inactive ingredients

corn starch, crospovidone, FD&C red #40 aluminum lake, FD&C yellow #6 aluminum lake, magnesium stearate, maltodextrin, microcrystalline cellulose, polyethylene glycol, polysorbate 80, polyvinyl alcohol, povidone, silicon dioxide, sodium starch glycolate, stearic acid, talc, titanium dioxide

Questions or comments?

1-877-507-6516

Principal display panel

24/7 life
BY 7-ELEVEn™

Cold & Flu
DayTime Severe

Acetaminophen / Pain Reliever/Fever Reducer
Dextromethorphan HBr / Cough Suppressant
Guaifenesin / Expectorant
Phenylephrine HCl / Nasal Decongestant

Relieves: Headache, Fever, Sore Throat,
Minor Aches & Pains, Chest Congestion,
Thins & Loosens Mucus, Nasal Congestion,
Sinus Pressure, Cough

compare to Vicks® DayQuil®
VapoCOOL™ SEVERE Cold &
Flu + Congestion active ingredients*

16
CAPLETS

Actual Size

TAMPER EVIDENT: DO NOT USE IF PACKAGE IS
OPENED OR IF BLISTER UNIT IS TORN, BROKEN
OR SHOWS ANY SIGNS OF TAMPERING

PARENTS:
Learn about teen medicine abuse
www.StopMedicineAbuse.org

Distributed by: 7-Eleven, Inc.
Irving, TX 75063 www.7-ELEVEN.com

Satisfaction Guaranteed 1-800-255-0711

*This product is not manufactured or
distributed by The Procter & Gamble Company. Vicks®,
DayQuil®, and VapoCOOL™ are trademarks of The Procter
& Gamble Company.

50844 REV0722A64021 65158C-SE-10-22

Convenience Valet 44-640